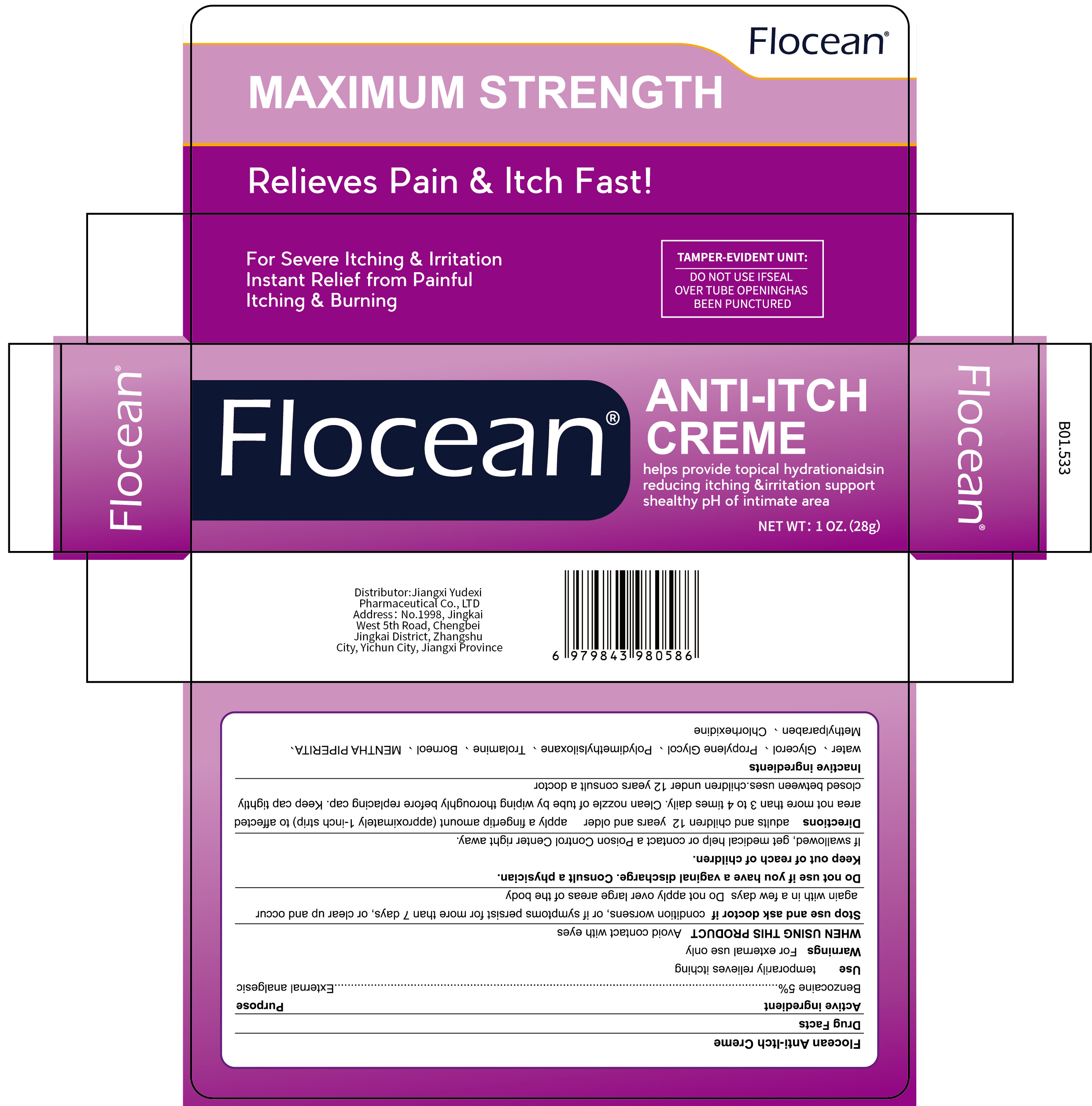 DRUG LABEL: Flocean ANTI-ITCH
NDC: 85248-094 | Form: CREAM
Manufacturer: Jiangxi Yudexi Pharmaceutical Co., LTD
Category: otc | Type: HUMAN OTC DRUG LABEL
Date: 20260207

ACTIVE INGREDIENTS: BENZOCAINE 5 g/100 g
INACTIVE INGREDIENTS: METHYLPARABEN; TROLAMINE; GLYCERIN; PROPYLENE GLYCOL; BORNEOL; DIMETHICONE; CHLORHEXIDINE; WATER; MENTHA PIPERITA

85248-094

Active Ingredient

Benzocaine 5%

Purpose

External analgesic

Use

temporarily relieves itching

Warnings

For external use only

Do not use

if you have a vaginal discharge. Consult a physician.

When Using

Avoid contact with eyes

Stop Use

condition worsens, or if symptoms persist for more than 7 days, or clear up and occur again with in a few days Do not apply over large areas of the body

Ask Doctor

condition worsens, or if symptoms persist for more than 7 days, or clear up and occur again with in a few days Do not apply over large areas of the body

Keep Oot Of Reach Of Children

If swallowed, get medical help or contact a Poison Control Center right away.

Directions

adults and children 12 years and older apply a fingertip amount (approximately 1-inch strip) to affected area not more than 3 to 4 times daily. Clean nozzle of tube by wiping thoroughly before replacing cap.Keep cap tightly closed between uses.

Other information

children under 12 years consult a doctor

Inactive ingredients

water 、Glycerol 、Propylene Glycol 、Polydimethylsiloxane 、Trolamine、Borneol、MENTHAPIPERITA、Methylparaben 、Chlorhexidine